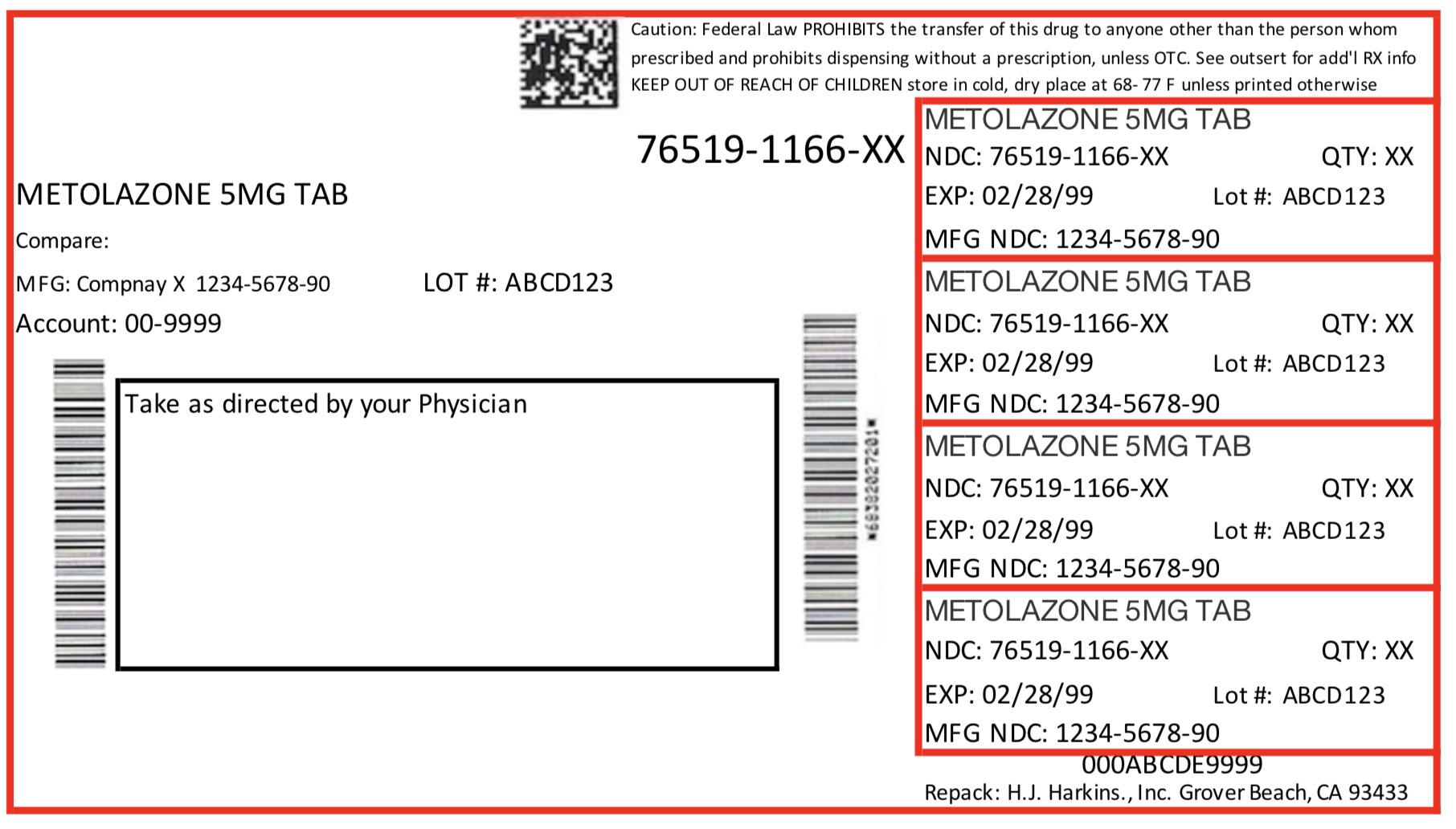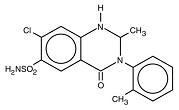 DRUG LABEL: METOLAZONE
NDC: 76519-1166 | Form: TABLET
Manufacturer: H.J. Harkins Co., Inc.
Category: prescription | Type: HUMAN PRESCRIPTION DRUG LABEL
Date: 20180326

ACTIVE INGREDIENTS: METOLAZONE 5 mg/1 1
INACTIVE INGREDIENTS: MAGNESIUM STEARATE; FD&C BLUE NO. 2; CELLULOSE, MICROCRYSTALLINE

Description

Upstate's metolazone tablets, USP, for oral administration contain 2½, 5, or 10 mg of metolazone, USP, a diuretic/saluretic/antihypertensive drug of the quinazoline class.

Metolazone has the molecular formula C16H16ClN3O3S, the chemical name 7-chloro-1, 2, 3, 4-tetrahydro-2-methyl-3-(2-methylphenyl)-4-oxo-6-quinazolinesulfonamide, and a molecular weight of 365.83. The structural formula is:

Metolazone is only sparingly soluble in water, but more soluble in plasma, blood, alkali, and organic solvents.

Inactive Ingredients: Magnesium stearate, microcrystalline cellulose and dye: 2½ mg-D&C Red No. 33; 5 mg-FD&C Blue No. 2; 10 mg-D&C Yellow No. 10 and FD&C Yellow No. 6.

Clinical Pharmacology

Metolazone is a quinazoline diuretic, with properties generally similar to the thiazide diuretics. The actions of metolazone result from interference with the renal tubular mechanism of electrolyte reabsorption. Metolazone acts primarily to inhibit sodium reabsorption at the cortical diluting site and to a lesser extent in the proximal convoluted tubule. Sodium and chloride ions are excreted in approximately equivalent amounts. The increased delivery of sodium to the distal tubular exchange site results in increased potassium excretion. Metolazone does not inhibit carbonic anhydrase. A proximal action of metolazone has been shown in humans by increased excretion of phosphate and magnesium ions and by a markedly increased fractional excretion of sodium in patients with severely compromised glomerular filtration. This action has been demonstrated in animals by micropuncture studies.

When Upstate's metolazone tablets, USP, are given, diuresis and saluresis usually begin within one hour and may persist for 24 hours or more. For most patients, the duration of effect can be varied by adjusting the daily dose. High doses may prolong the effect. A single daily dose is recommended. When a desired therapeutic effect has been obtained, it may be possible to reduce dosage to a lower maintenance level.

The diuretic potency of metolazone tablets, USP, at maximum therapeutic dosage is approximately equal to thiazide diuretics. However, unlike thiazides, metolazone tablets, USP, may produce diuresis in patients with glomerular filtration rates below 20 mL/min.

Metolazone tablets, USP, and furosemide administered concurrently have produced marked diuresis in some patients where edema or ascites was refractory to treatment with maximum recommended doses of these or other diuretics administered alone. The mechanism of this interaction is unknown (see WARNINGS and PRECAUTIONS, DRUG INTERACTIONS).

Maximum blood levels of metolazone are found approximately eight hours after dosing. A small fraction of metolazone is metabolized. Most of the drug is excreted in the unconverted form in the urine.

Indications & Usage

Upstate's metolazone tablets, USP, are indicated for the treatment of salt and water retention including:

edema accompanying congestive heart failure;
edema accompanying renal diseases, including the nephrotic syndrome and states of diminished renal function.

Metolazone tablets, USP, are also indicated for the treatment of hypertension, alone or in combination with other antihypertensive drugs of a different class. MYKROX Tablets, a more rapidly available form of metolazone, are intended for the treatment of new patients with mild to moderate hypertension. A dose titration is necessary if MYKROX Tablets are to be substituted for Upstate's metolazone tablets, USP, in the treatment of hypertension. See package circular for MYKROX Tablets (UCB).

Usage In Pregnancy

The routine use of diuretics in an otherwise healthy woman is inappropriate and exposes mother and fetus to unnecessary hazard. Diuretics do not prevent development of toxemia of pregnancy, and there is no evidence that they are useful in the treatment of developed toxemia.

Edema during pregnancy may arise from pathologic causes or from the physiologic and mechanical consequences of pregnancy. Metolazone tablets, USP, are indicated in pregnancy when edema is due to pathologic causes, just as it is in the absence of pregnancy (see PRECAUTIONS). Dependent edema in pregnancy resulting from restriction of venous return by the expanded uterus is properly treated through elevation of the lower extremities and use of support hose; use of diuretics to lower intravascular volume in this case is illogical and unnecessary. There is hypervolemia during normal pregnancy which is harmful to neither the fetus nor the mother (in the absence of cardiovascular disease), but which is associated with edema, including generalized edema, in the majority of pregnant women. If this edema produces discomfort, increased recumbency will often provide relief. In rare instances, this edema may cause extreme discomfort which is not relieved by rest. In these cases, a short course of diuretics may be appropriate.

Contraindications

Anuria, hepatic coma or precoma, known allergy or hypersensitivity to metolazone.

Warnings

Rapid Onset Hyponatremia And/Or Hypokalemia

Rarely, the rapid onset of severe hyponatremia and/or hypokalemia has been reported following initial doses of thiazide and non-thiazide diuretics. When symptoms consistent with severe electrolyte imbalance appear rapidly, drug should be discontinued and supportive measures should be initiated immediately. Parenteral electrolytes may be required. Appropriateness of therapy with this class of drugs should be carefully reevaluated.

Hypokalemia

Hypokalemia may occur with consequent weakness, cramps, and cardiac dysrhythmias. Serum potassium should be determined at regular and appropriate intervals, and dose reduction, potassium supplementation or addition of a potassium-sparing diuretic instituted whenever indicated. Hypokalemia is a particular hazard in patients who are digitalized or who have or have had a ventricular arrhythmia; dangerous or fatal arrhythmias may be precipitated. Hypokalemia is dose related.

Concomitant Therapy

Lithium

In general, diuretics should not be given concomitantly with lithium because they reduce its renal clearance and add a high risk of lithium toxicity. Read prescribing information for lithium preparations before use of such concomitant therapy.

Furosemide

Unusually large or prolonged losses of fluids and electrolytes may result when metolazone tablets, USP, are administered concomitantly to patients receiving furosemide (see PRECAUTIONS, DRUG INTERACTIONS).

Other Antihypertensive Drugs

When metolazone tablets, USP, are used with other antihypertensive drugs, particular care must be taken to avoid excessive reduction of blood pressure, especially during initial therapy.

Cross-Allergy

Cross-allergy may occur when metolazone tablets, USP, are given to patients known to be allergic to sulfonamide-derived drugs, thiazides, or quinethazone.

Sensitivity Reactions

Sensitivity reactions (e.g., angioedema, bronchospasm) may occur with or without a history of allergy or bronchial asthma and may occur with the first dose of metolazone tablets, USP.

Precautions

DO NOT INTERCHANGE

DO NOT INTERCHANGE UPSTATE'S METOLAZONE TABLETS, USP, ZAROXOLYN TABLETS, AND OTHER FORMULATIONS OF METOLAZONE THAT SHARE THEIR SLOW AND INCOMPLETE BIOAVAILABILITY AND ARE NOT THERAPEUTICALLY EQUIVALENT AT THE SAME DOSES TO MYKROX TABLETS, A MORE RAPIDLY AVAILABLE AND COMPLETELY BIOAVAILABLE METOLAZONE PRODUCT. FORMULATIONS BIOEQUIVALENT TO ZAROXOLYN AND FORMULATIONS BIOEQUIVALENT TO MYKROX SHOULD NOT BE INTERCHANGED FOR ONE ANOTHER.

General

Fluid And Electrolytes

All patients receiving therapy with metolazone tablets, USP, should have serum electrolyte measurements done at appropriate intervals and be observed for clinical signs of fluid and/or electrolyte imbalance: namely, hyponatremia, hypochloremic alkalosis, and hypokalemia. In patients with severe edema accompanying cardiac failure or renal disease, a low-salt syndrome may be produced, especially with hot weather and a low-salt diet. Serum and urine electrolyte determinations are particularly important when the patient has protracted vomiting, severe diarrhea, or is receiving parenteral fluids. Warning signs of imbalance are: dryness of mouth, thirst, weakness, lethargy, drowsiness, restlessness, muscle pains or cramps, muscle fatigue, hypotension, oliguria, tachycardia, and gastrointestinal disturbances such as nausea and vomiting. Hyponatremia may occur at any time during long term therapy and, on rare occasions, may be life threatening.

The risk of hypokalemia is increased when larger doses are used, when diuresis is rapid, when severe liver disease is present, when corticosteroids are given concomitantly, when oral intake is inadequate or when excess potassium is being lost extrarenally, such as with vomiting or diarrhea.

Thiazide-like diuretics have been shown to increase the urinary excretion of magnesium; this may result in hypomagnesemia.

Glucose Tolerance

Metolazone may raise blood glucose concentrations possibly causing hyperglycemia and glycosuria in patients with diabetes or latent diabetes.

Hyperuricemia

Metolazone tablets, USP, regularly cause an increase in serum uric acid and can occasionally precipitate gouty attacks even in patients without a prior history of them.

Azotemia

Azotemia, presumably prerenal azotemia, may be precipitated during the administration of metolazone tablets, USP. If azotemia and oliguria worsen during treatment of patients with severe renal disease, metolazone tablets, USP, should be discontinued.

Renal Impairment

Use caution when administering metolazone tablets, USP, to patients with severely impaired renal function. As most of the drug is excreted by the renal route, accumulation may occur.

Orthostatic Hypotension

Orthostatic hypotension may occur; this may be potentiated by alcohol, barbiturates, narcotics, or concurrent therapy with other antihypertensive drugs.

Hypercalcemia

Hypercalcemia may infrequently occur with metolazone, especially in patients taking high doses of vitamin D or with high bone turnover states, and may signify hidden hyperparathyroidism. Metolazone should be discontinued before tests for parathyroid function are performed.

Systemic Lupus Erythematosus

Thiazide diuretics have exacerbated or activated systemic lupus erythematosus and this possibility should be considered with metolazone tablets, USP.

Information For Patients

Patients should be informed of possible adverse effects, advised to take the medication as directed, and promptly report any possible adverse reactions to the treating physician.

Drug Interactions

Diuretics

Furosemide and probably other loop diuretics given concomitantly with metolazone can cause unusually large or prolonged losses of fluid and electrolytes (see WARNINGS).

Other Antihypertensives

When metolazone tablets, USP, are used with other antihypertensive drugs, care must be taken, especially during initial therapy. Dosage adjustments of other antihypertensives may be necessary.

Alcohol, Barbiturates, And Narcotics

The hypotensive effects of these drugs may be potentiated by the volume contraction that may be associated with metolazone therapy.

Digitalis Glycosides

Diuretic-induced hypokalemia can increase the sensitivity of the myocardium to digitalis. Serious arrhythmias can result.

Corticosteroids Or ACTH

May increase the risk of hypokalemia and increase salt and water retention.

Lithium

Serum lithium levels may increase (see WARNINGS).

Curariform Drugs

Diuretic-induced hypokalemia may enhance neuromuscular blocking effects of curariform drugs (such as tubocurarine) – the most serious effect would be respiratory depression which could proceed to apnea. Accordingly, it may be advisable to discontinue metolazone tablets, USP, three days before elective surgery.

Salicylates And Other Non-Steroidal Anti-Inflammatory Drugs

May decrease the antihypertensive effects of metolazone tablets, USP.

Sympathomimetics

Metolazone may decrease arterial responsiveness to norepinephrine, but this diminution is not sufficient to preclude effectiveness of the pressor agent for therapeutic use.

Insulin And Oral Antidiabetic Agents

See GLUCOSE TOLERANCE UNDER PRECAUTIONS, GENERAL.

Methenamine

Efficacy may be decreased due to urinary alkalizing effect of metolazone.

Anticoagulants

Metolazone, as well as other thiazide-like diuretics, may affect the hypoprothrombinemic response to anticoagulants; dosage adjustments may be necessary.

Drug/Laboratory Test Interactions

None reported.

Carcinogenesis, Mutagenesis, Impairment Of Fertility

Mice and rats administered metolazone 5 days/week for up to 18 and 24 months, respectively, at daily doses of 2, 10, and 50 mg/kg, exhibited no evidence of a tumorigenic effect of the drug. The small number of animals examined histologically and poor survival in the mice limit the conclusions that can be reached from these studies.

Metolazone was not mutagenic in vitro in the Ames Test using Salmonella typhimurium strains TA-97, TA-98, TA-100, TA-102, and TA-1535.

Reproductive performance has been evaluated in mice and rats. There is no evidence that metolazone possesses the potential for altering reproductive capacity in mice. In a rat study, in which males were treated orally with metolazone at doses of 2, 10, and 50 mg/kg for 127 days prior to mating with untreated females, an increased number of resorption sites was observed in dams mated with males from the 50 mg/kg group. In addition, the birth weight of offspring was decreased and the pregnancy rate was reduced in dams mated with males from the 10 and 50 mg/kg groups.

Pregnancy

Teratogenic Effects

Pregnancy Category B

Reproduction studies performed in mice, rabbits, and rats treated during the appropriate period of gestation at doses up to 50 mg/kg/day have revealed no evidence of harm to the fetus due to metolazone. There are, however, no adequate and well-controlled studies in pregnant women. Because animal reproduction studies are not always predictive of human response, metolazone tablets, USP, should be used during pregnancy only if clearly needed. Metolazone crosses the placental barrier and appears in cord blood.

Non-Teratogenic Effects

The use of metolazone tablets, USP, in pregnant women requires that the anticipated benefit be weighed against possible hazards to the fetus. These hazards include fetal or neonatal jaundice, thrombocytopenia, and possibly other adverse reactions which have occurred in the adult. It is not known what effect the use of the drug during pregnancy has on the later growth, development, and functional maturation of the child. No such effects have been reported with metolazone.

Labor And Delivery

Based on clinical studies in which women received metolazone in late pregnancy until the time of delivery, there is no evidence that the drug has any adverse effects on the normal course of labor or delivery.

Nursing Mothers

Metolazone appears in breast milk. Because of the potential for serious adverse reactions in nursing infants from metolazone, a decision should be made whether to discontinue nursing or to discontinue the drug, taking into account the importance of the drug to the mother.

Pediatric Use

Safety and effectiveness in pediatric patients have not been established in controlled clinical trials. There is limited experience with the use of Upstate's metolazone tablets, USP, in pediatric patients with congestive heart failure, hypertension, bronchopulmonary dysplasia, nephrotic syndrome and nephrogenic diabetes insipidus. Doses used generally ranged from 0.05 to 0.1 mg/kg administered once daily and usually resulted in a 1 to 2.8 kg weight loss and 150 to 300 cc increase in urine output. Not all patients responded and some gained weight. Those patients who did respond did so in the first few days of treatment. Prolonged use (beyond a few days) was generally associated with no further beneficial effect or a return to baseline status and is not recommended.

There is limited experience with the combination of metolazone tablets, USP, and furosemide in pediatric patients with furosemide-resistant edema. Some benefited while others did not or had an exaggerated response with hypovolemia, tachycardia, and orthostatic hypotension requiring fluid replacement. Severe hypokalemia was reported and there was a tendency for diuresis to persist for up to 24 hours after metolazone tablets, USP, were discontinued. Hyperbilirubinemia has been reported in 1 neonate. Close clinical and laboratory monitoring of all children treated with diuretics is indicated. See CONTRAINDICATIONS, WARNINGS, PRECAUTIONS.

Geriatric Use

Clinical studies of metolazone tablets, USP, did not include sufficient numbers of subjects aged 65 and over to determine whether they respond differently from younger subjects. Other reported clinical experience has not identified differences in responses between the elderly and younger patients. In general, dose selection for an elderly patient should be cautious, usually starting at the low end of the dosing range, reflecting the greater frequency of decreased hepatic, renal, or cardiac function, and of concomitant disease or other drug therapy.

This drug is known to be substantially excreted by the kidney, and the risk of toxic reactions to this drug may be greater in patients with impaired renal function. Because elderly patients are more likely to have decreased renal function, care should be taken in dose selection, and it may be useful to monitor renal function.

Adverse Reactions

Metolazone tablets, USP, are usually well tolerated, and most reported adverse reactions have been mild and transient. Many of metolazone tablets, USP, related adverse reactions represent extensions of its expected pharmacologic activity and can be attributed to either its antihypertensive action or its renal/metabolic actions. The following adverse reactions have been reported. Several are single or comparably rare occurrences. Adverse reactions are listed in decreasing order of severity within body systems.

Cardiovascular

Chest pain/discomfort, orthostatic hypotension, excessive volume depletion, hemoconcentration, venous thrombosis, palpitations.

Central And Peripheral Nervous System

Syncope, neuropathy, vertigo, paresthesias, psychotic depression, impotence, dizziness/lightheadedness, drowsiness, fatigue, weakness, restlessness (sometimes resulting in insomnia), headache.

Dermatologic/Hypersensitivity

Toxic epidermal necrolysis (TEN), Stevens-Johnson Syndrome, necrotizing angiitis (cutaneous vasculitis), skin necrosis, purpura, petechiae, dermatitis (photosensitivity), urticaria, pruritus, skin rashes.

Gastrointestinal

Hepatitis, intrahepatic cholestatic jaundice, pancreatitis, vomiting, nausea, epigastric distress, diarrhea, constipation, anorexia, abdominal bloating, abdominal pain.

Hematologic

Aplastic/hypoplastic anemia, agranulocytosis, leukopenia, thrombocytopenia.

Metabolic

Hypokalemia, hyponatremia, hyperuricemia, hypochloremia, hypochloremic alkalosis, hyperglycemia, glycosuria, increase in serum urea nitrogen (BUN) or creatinine, hypophosphatemia, hypomagnesemia, hypercalcemia.

Musculoskeletal

Joint pain, acute gouty attacks, muscle cramps or spasm.

Other

Transient blurred vision, chills, dry mouth.

In addition, adverse reactions reported with similar antihypertensive-diuretics, but which have not been reported to date for metolazone tablets, USP, include: bitter taste, sialadenitis, xanthopsia, respiratory distress (including pneumonitis), and anaphylactic reactions. These reactions should be considered as possible occurrences with clinical usage of metolazone tablets, USP.

Whenever adverse reactions are moderate or severe, metolazone tablets, USP, dosage should be reduced or therapy withdrawn.

Overdosage

Intentional overdosage has been reported rarely with metolazone and similar diuretic drugs.

Signs And Symptoms

Orthostatic hypotension, dizziness, drowsiness, syncope, electrolyte abnormalities, hemoconcentration and hemodynamic changes due to plasma volume depletion may occur. In some instances depressed respiration may be observed. At high doses, lethargy of varying degree may progress to coma within a few hours. The mechanism of CNS depression with thiazide overdosage is unknown. Also, GI irritation and hypermotility may occur. Temporary elevation of BUN has been reported, especially in patients with impairment of renal function. Serum electrolyte changes and cardiovascular and renal function should be closely monitored.

Treatment

There is no specific antidote available but immediate evacuation of stomach contents is advised. Dialysis is not likely to be effective. Care should be taken when evacuating the gastric contents to prevent aspiration, especially in the stuporous or comatose patient. Supportive measures should be initiated as required to maintain hydration, electrolyte balance, respiration, and cardiovascular and renal function.

Dosage & Administration

ffective dosage of Upstate's metolazone tablets, USP, should be individualized according to indication and patient response. A single daily dose is recommended. Therapy with metolazone tablets, USP, should be titrated to gain an initial therapeutic response and to determine the minimal dose possible to maintain the desired therapeutic response.

Usual Single Daily Dosage Schedules

Suitable initial dosages will usually fall in the ranges given.

Edema of cardiac failure:

Metolazone tablets, USP, 5 to 20 mg once daily.

Edema of renal disease:

Metolazone tablets, USP, 5 to 20 mg once daily.

Mild to moderate essential hypertension:

Metolazone tablets, USP, 2½ to 5 mg once daily.

New patients – MYKROX Tablets (metolazone tablets, USP) (see MYKROX package circular). If considered desirable to switch patients currently on Upstate's metolazone tablets, USP, to MYKROX, the dose should be determined by titration starting at one tablet (½ mg) once daily and increasing to two tablets (1 mg) once daily if needed.

Treatment Of Edematous States

The time interval required for the initial dosage to produce an effect may vary. Diuresis and saluresis usually begin within one hour and persist for 24 hours or longer. When a desired therapeutic effect has been obtained, it may be advisable to reduce the dose if possible. The daily dose depends on the severity of the patient's condition, sodium intake, and responsiveness. A decision to change the daily dose should be based on the results of thorough clinical and laboratory evaluations. If antihypertensive drugs or diuretics are given concurrently with metolazone tablets, USP, more careful dosage adjustment may be necessary. For patients who tend to experience paroxysmal nocturnal dyspnea, it may be advisable to employ a larger dose to ensure prolongation of diuresis and saluresis for a full 24-hour period.

Treatment Of Hypertension

The time interval required for the initial dosage regimen to show effect may vary from three or four days to three to six weeks in the treatment of elevated blood pressure. Doses should be adjusted at appropriate intervals to achieve maximum therapeutic effect.

How supplied

Upstate's metolazone tablets, USP, are shallow biconvex, round tablets, and are available in three strengths:

5 mg, blue, debossed "644" on one side, and "5" on reverse side.

Storage

Store at 25°C (77°F); excursions permitted to 15°-30°C (59°-86°F) [See USP Controlled Room Temperature].

Protect from light. Keep out of the reach of children.

For more information about Metolazone Tablets, USP call 1-844-599-CARE (2273).